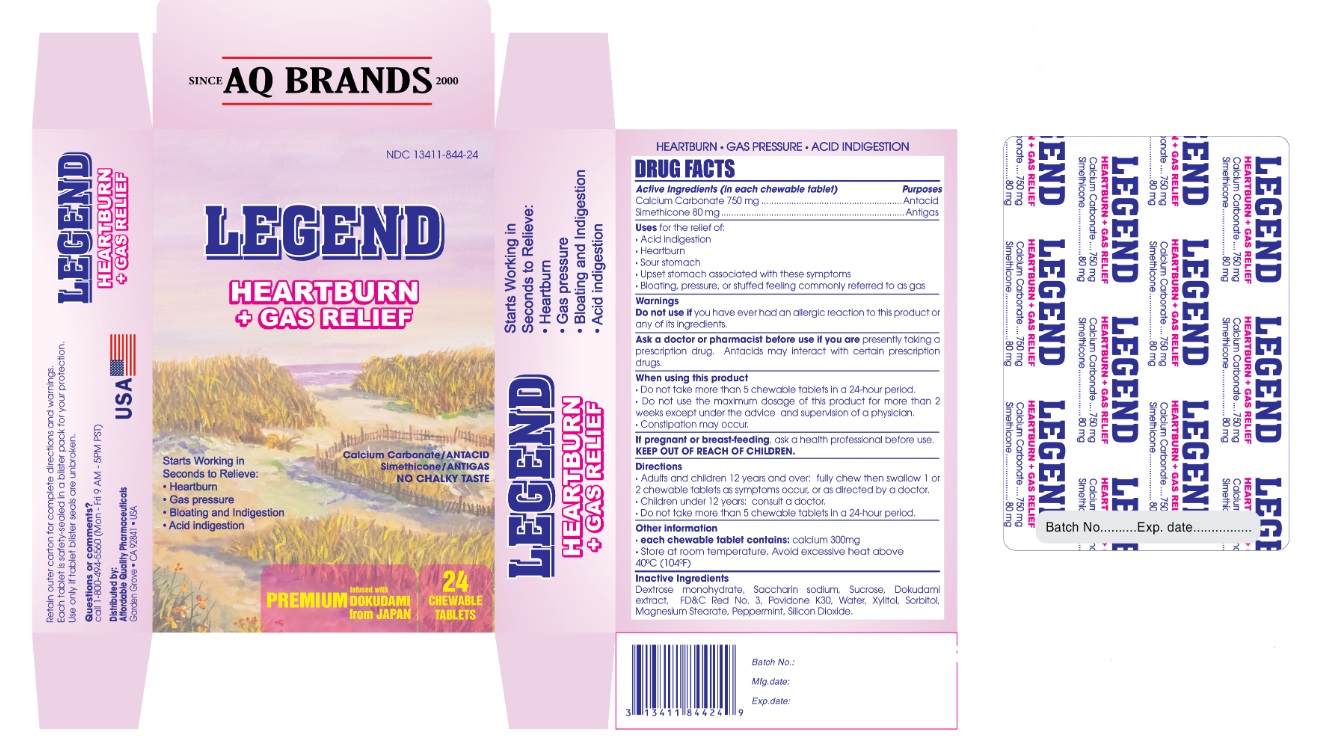 DRUG LABEL: LEGEND PREMIUM HEARTBURN CHEWABLE
NDC: 13411-844 | Form: TABLET
Manufacturer: ADVANCED PHARMACEUTICAL SERVICES, INC. DBA AFFORDABLE QUALITY PHARMACEUTICALS
Category: otc | Type: HUMAN OTC DRUG LABEL
Date: 20200622

ACTIVE INGREDIENTS: CALCIUM CARBONATE 750 mg/1 1; DIMETHICONE 80 mg/1 1
INACTIVE INGREDIENTS: DEXTROSE MONOHYDRATE; SACCHARIN SODIUM; SUCROSE; HOUTTUYNIA CORDATA FLOWERING TOP; FD&C RED NO. 3; POVIDONE K30; WATER; XYLITOL; SORBITOL; MAGNESIUM STEARATE; PEPPERMINT; SILICON DIOXIDE

LEGEND PREMIUM HEARTBURN GAS RELIEF CHEWABLE

Active Ingredients

Calcium carbonate 750 mg.

Simethicone 80 mg.

Purpose

- Antacid
- Antigas

Warnings

Do not use if you have ever had an allergic reaction to this product or any of its ingredients

Ask a doctor or pharmacist before use if you are presently taking a prescription drug. Antacids may interact with certain prescription drugs.

When using this product
● Do not take more than 5 chewable tablets in a 24-hour period
● Do not use the maximum dosage of this product for more than 2 weeks except under the advice and supervision of a physician
● Constipation may occur

If pregnant or breast-feeding, ask a health professional before use.
.

Uses for the relief of

● acid indigestion
● heartburn
● sour stomach
● upset stomach associated with these symptoms
● bloating, pressure, or stuffed feeling commonly referred to as gas

Directions

● adults and children 12 years and over: fully chew then swallow 1 or 2 chewable tablets as symptoms occur, or as directed by a doctor.
● children under 12 years: consult a doctor
● do not take more than 5 chewable tablets in a 24-hour period.

Other information

● each chewable tablet contains: calcium 300 mg
● store at room temperature. Avoid excessive heat above 40oC (104 F).

Inactive Ingredients

Dextrose monohydrate, Saccharin sodium, Sucrose, Dokudami extract, FD&C Red No. 3, Povidone K30, Water, Xylitol, Sorbitol, Magnesium Stearate, Peppermint, Silicon Dioxide